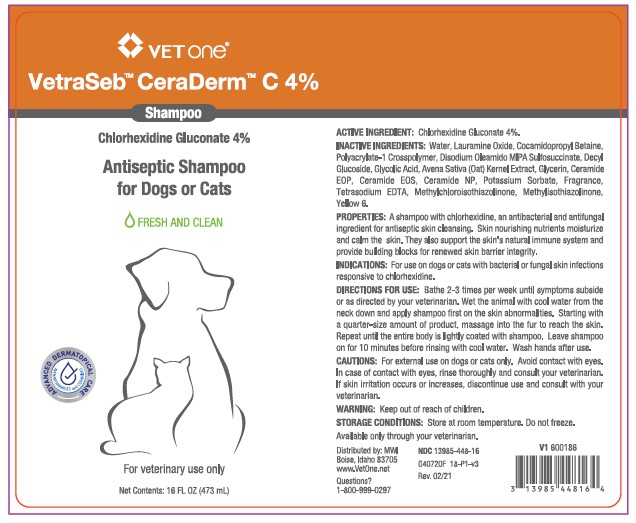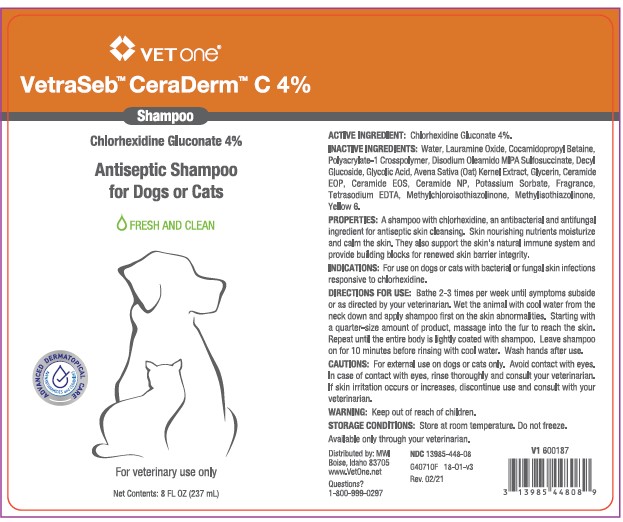 DRUG LABEL: VetraSeb CeraDerm
NDC: 13985-448 | Form: SHAMPOO
Manufacturer: MWI/VetOne
Category: animal | Type: OTC ANIMAL DRUG LABEL
Date: 20210407

ACTIVE INGREDIENTS: CHLORHEXIDINE GLUCONATE 40 mg/1 mL
INACTIVE INGREDIENTS: WATER; LAURAMINE OXIDE; COCAMIDOPROPYL BETAINE; CARBOMER HOMOPOLYMER, UNSPECIFIED TYPE; DISODIUM OLEAMIDO MIPA-SULFOSUCCINATE; DECYL GLUCOSIDE; GLYCOLIC ACID; AVENANTHRAMIDES; GLYCERIN; CERAMIDE 1; CERAMIDE EOS; CERAMIDE NP; POTASSIUM SORBATE; EDETATE SODIUM; METHYLCHLOROISOTHIAZOLINONE; METHYLISOTHIAZOLINONE

DESCRIPTION

VetraSeb™ CeraDerm™C 4%

Shampoo

Chlorhexidine Gluconate 4%

Antiseptic Shampoo for Dogs or Cats

FRESH AND CLEAN

For veterinary use only

ACTIVE INGREDIENT: Chlorhexidine Gluconate 4%

INACTIVE INGREDIENTS: Water, Lauramine Oxide, Cocamidopropyl Betaine, Polyacrylate-1 Crosspolymer, Disodium Oleamido MIPA Sulfosuccinate, Decyl Glucoside, Glycolic Acid, Avena Sativa (Oat) Kernal Extract, Glycerin, Ceramide EOS, Ceramide EOP, Ceramide NP, Potassium Sorbate, Fragrance, Tetrasodium EDTA, Sodium Chloride, Methylchloroisothiazolinone, Methylisothiazolinone.

PROPERTIES: A shampoo with chlorhexidine, an antibacterial and antifungal ingredient for antiseptic skin cleansing. Skin nourishing nutrients moisturize and calm the skin. They also support the skin's natural immune system and provide building blocks for renewed skin barrier integrity.

INDICATIONS AND USAGE

INDICATIONS: For use on dogs or cats with bacterial or fungal skin infections responsive to chlorhexidine.

DIRECTIONS FOR USE: Bathe 2-3 times per week until symptoms subside or as directed by your veterinarian. Wet the animal with cool water from the neck down and apply the shampoo first on the skin abnormalities. Starting with a quarter-size amount of product, massage in the fur to reach the skin. Repeat until the entire body is lightly coated with shampoo. Leave shampoo on for 10 minutes before rinsing with cool water. Wash hands after use.

WARNINGS AND PRECAUTIONS

CAUTIONS: For external use on dogs or cats only. Avoid contact with eyes. In case of contact with eyes, rinse thoroughly and consult your veterinarian. If skin irritation occurs or increases, discontinue use and consult your veterinarian.

WARNING: Keep out of the reach of children.

STORAGE AND HANDLING

STORAGE CONDITIONS: Store at room temperature. Do not freeze.

Available through your veterinarian.

Distributed by: MWI

Boise, Idaho 83705

www.VetOne.net

Questions?

1-800-999-0297

PRINCIPAL DISPLAY PANEL - 8 OUNCE (237 mL) Bottle

VETONE®

VetraSeb™ CeraDerm™ C 4%

Shampoo

Chlorhexidine Gluconate 4%

Antiseptic Shampoo

for Dogs or Cats

FRESH AND CLEAN

For veterinary use only

Net Contents: 8 FL. OZ. (237 mL)

PRINCIPAL DISPLAY PANEL - 16 OUNCE (473 mL) Bottle

VETONE®

VetraSeb™ CeraDerm™ C 4%

Shampoo

Chlorhexidine Gluconate 4%

Antiseptic Shampoo
for Dogs or Cats

FRESH AND CLEAN

For veterinary use only

Net Content: 16 FL. OZ. (473 mL)